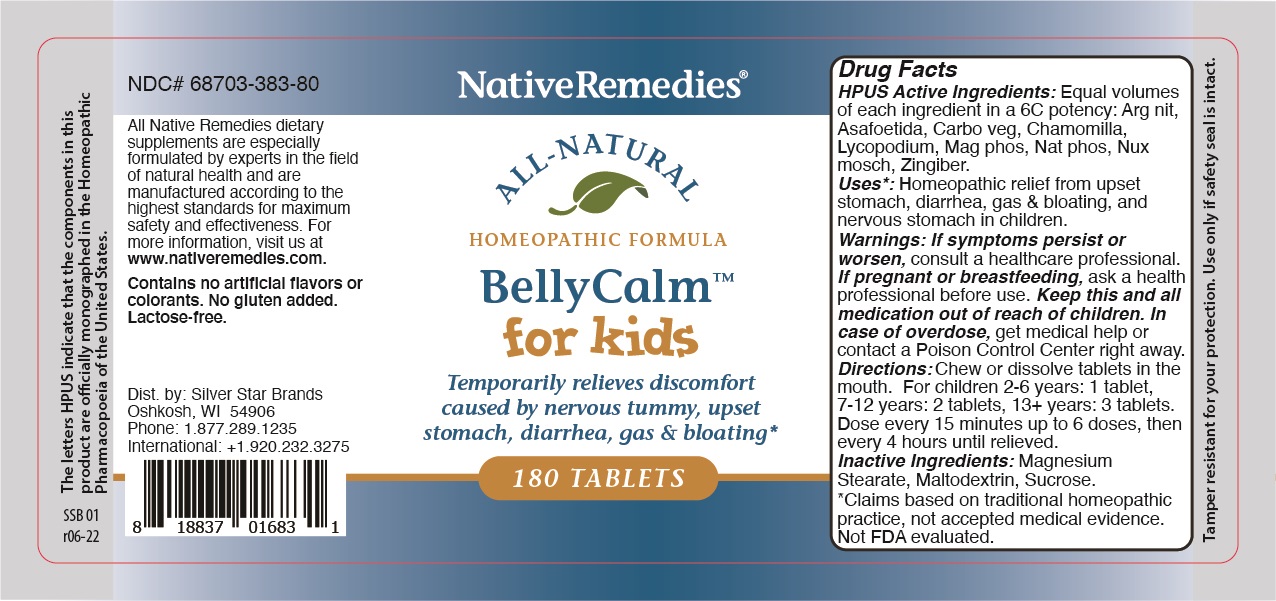 DRUG LABEL: Belly Calm
NDC: 68703-383 | Form: TABLET
Manufacturer: Silver Star Brands
Category: homeopathic | Type: HUMAN OTC DRUG LABEL
Date: 20250101

ACTIVE INGREDIENTS: FERULA SUMBUL ROOT 6 [hp_C]/1 1; MATRICARIA RECUTITA 6 [hp_C]/1 1; LYCOPODIUM CLAVATUM SPORE 6 [hp_C]/1 1; NUTMEG 6 [hp_C]/1 1; GINGER 6 [hp_C]/1 1; SILVER NITRATE 6 [hp_C]/1 1; MAGNESIUM PHOSPHATE, DIBASIC TRIHYDRATE 6 [hp_C]/1 1; SODIUM PHOSPHATE, DIBASIC 6 [hp_C]/1 1; ACTIVATED CHARCOAL 6 [hp_C]/1 1
INACTIVE INGREDIENTS: MAGNESIUM STEARATE; MALTODEXTRIN; SUCROSE

Belly Calm for kids

HPUS Active Ingredients: Equal volumes of each ingredient in a 6C potency: Arg nit, Asafoetida, Carbo veg, Chamomilla, Lycopodium, Mag phos, Nat phos, Nux mosch, Zingiber.

The letters HPUS indicate that the components in this product are offically momographed in the Homeopathic Pharmacopoeia of the United States.

Uses*

Uses*: Homeopathic relief from upset stomach, diarrhea, gas & bloating, and nervous stomach in children.

*Claims based on traditional homeopathic practice, not accepted medical evidence. Not FDA evaluated.

Warnings

Warnings: If symptoms persist or worsen, consult a healthcare professional. If pregnant or breastfeeding, ask a health professional before use.

Keep this and all medication out of reach of children.

In case of overdose, get medical help or contact Poison Control Center right away.

Directions

Directions: Chew or dissolve tablets in the mouth. For children 2-6 years: 1 tablet, 7-12 years: 2 tablets, 13+ years: 3 tablets. Dose every 15 minutes up to 6 doses, then every 4 hours until relieved.

OTHER SAFETY INFORMATION

Contains no artificial flavors or colorants. No gluten added. Lactose-free.

Inactive Ingredients

Inactive ingredients: Magnesium Stearate, Maltodextin, Sucrose.

KEEP OUT OF REACH OF CHILDREN

Keep this and all medication out of reach of children.

PREGNANCY OR BREAST FEEDING

If pregnant or breast feeding, ask a health professional before use.

PURPOSE

Temporarily relieves discomfort caused by nervous tummy, upset stomach, diarrhea, gas & bloating.*